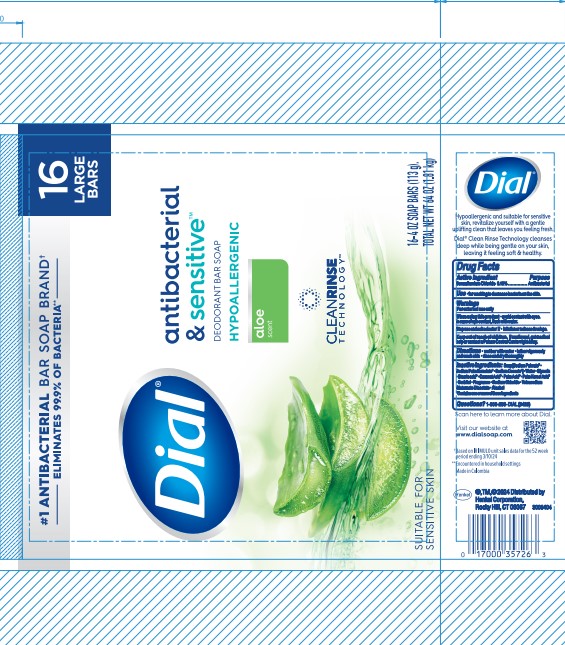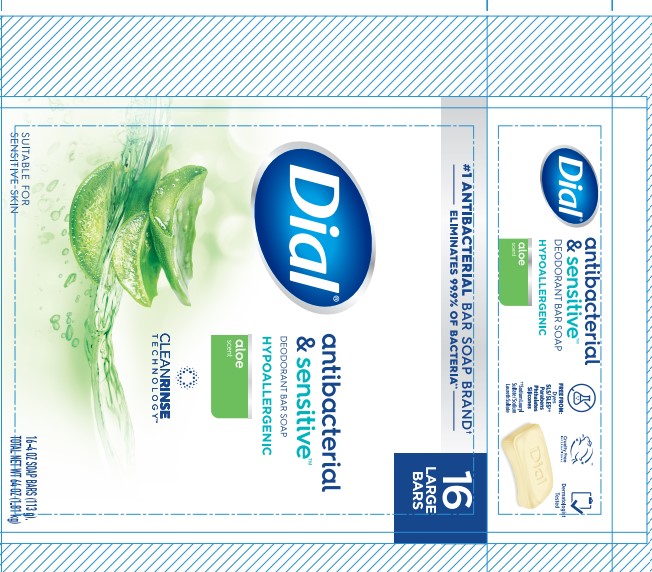 DRUG LABEL: Dial Antibacterial and Sensitive Aloe
NDC: 54340-267 | Form: SOAP
Manufacturer: Henkel Corporation
Category: otc | Type: HUMAN OTC DRUG LABEL
Date: 20251216

ACTIVE INGREDIENTS: BENZALKONIUM CHLORIDE 0.1 g/100 g
INACTIVE INGREDIENTS: ALCOHOL 0.01 g/100 g; SODIUM CHLORIDE 0.3898 g/100 g; SODIUM PALM KERNELATE; SORBITOL; GLYCERIN 8.1 g/100 g; SODIUM PALMATE 61.84 g/100 g; STEARIC ACID 2.435 g/100 g; WATER; TETRASODIUM GLUTAMATE DIACETATE 0.058 g/100 g

Dial Antibacterial& Sensitive Deodorant Bar Soap Hypoallergenic Aloe Scent

Drug Facts

Active ingredient

Benzalkonium Chloride 0.1%

Purpose

Antibacterial

Use

- for washing to decrease bacteria on the skin.

Warnings

For external use only

When using this product

- avoid contact with the eyes. In case of eye contact, flush with water.

Stop use and ask a doctor if

- irritation and redness develops.

Keep out of reach of children. If swallowed, get medical help or contact a Poison Control Center right away.

Directions

- wet bar with water
- lather vigorously and wash skin
- rinse and dry thoroughly

INACTIVE INGREDIENT

Inactive ingredients Soap[ Sodium Palmate* · Sodium Palm Kernelate* · Sodium Cocoate*] · Water · Glycerin · Stearic acid* · Coconut Acid* · Palm Acid* · Palm Kernel Acid* · Sorbitol · Fragrance · Sodium Chloride · Tetrasodium Glutamate Diacetate · Alcohol *Contains one or more of these ingredients

Questions? 1-800-258-DIAL (3425)

Visit our website at www.dialsoap.com

Made in Colombia

Henkel®, TM, ©2024 Distributed by

Henkel Corporation, Rocky Hill, CT 06067